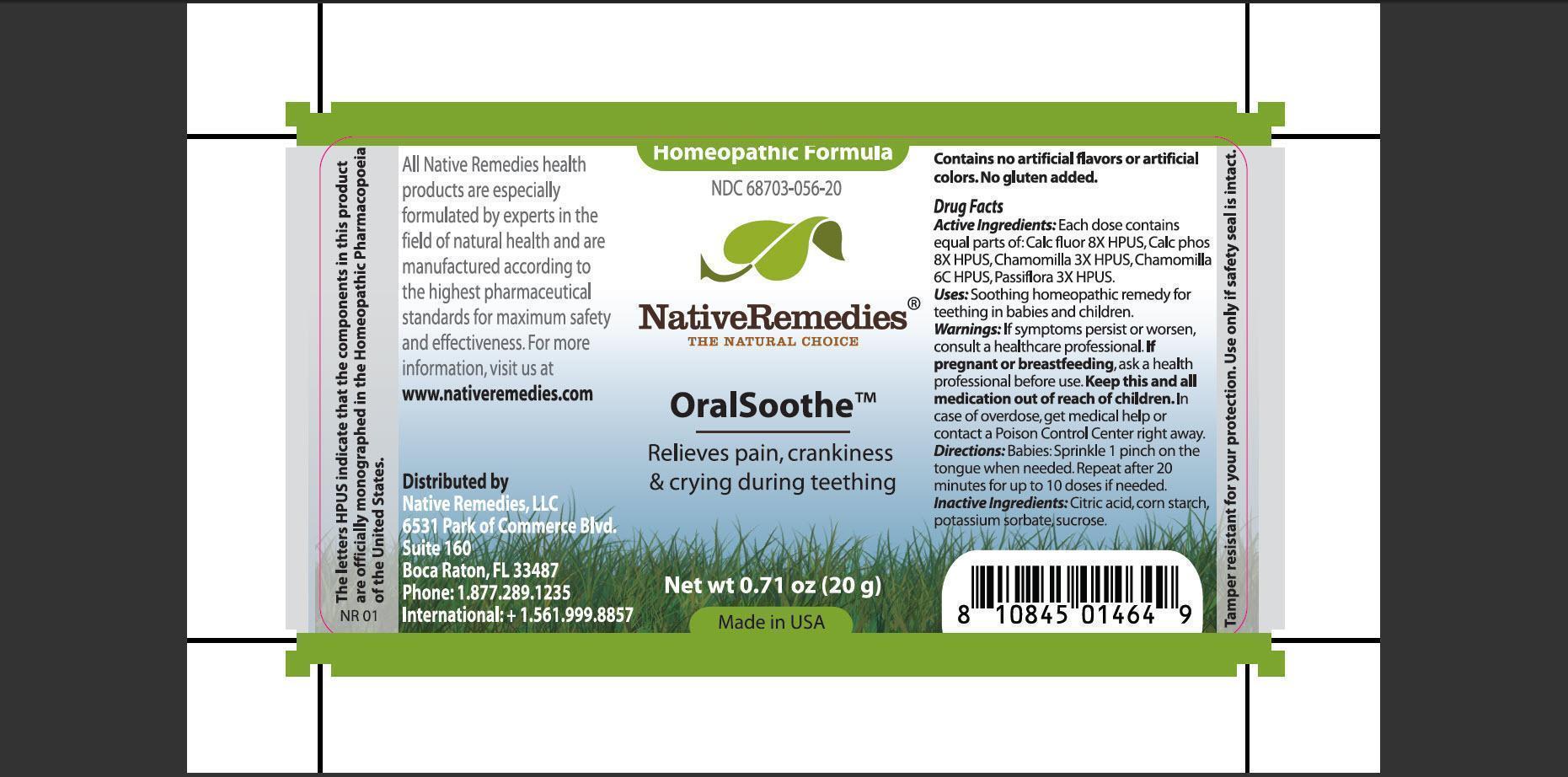 DRUG LABEL: OralSoothe
                
NDC: 68703-056 | Form: GRANULE
Manufacturer: Native Remedies, LLC
Category: homeopathic | Type: HUMAN OTC DRUG LABEL
Date: 20130108

ACTIVE INGREDIENTS: CALCIUM FLUORIDE 8 [hp_X]/16 mg; TRIBASIC CALCIUM PHOSPHATE 8 [hp_X]/16 mg; MATRICARIA RECUTITA 3 [hp_X]/16 mg; MATRICARIA RECUTITA 6 [hp_C]/16 mg; PASSIFLORA INCARNATA FLOWERING TOP 3 [hp_X]/16 mg
INACTIVE INGREDIENTS: CITRIC ACID MONOHYDRATE; STARCH, CORN; POTASSIUM SORBATE; SUCROSE

OralSoothe

PURPOSE

Relieves pain, crankiness & crying during teething

ACTIVE INGREDIENT

Active Ingredients: Each dose contains equal parts of: Calc fluor 8X HPUS, Calc phos 8X HPUS, Chamomilla 3X HPUS, Chamomilla 6C HPUS, Passiflora 3X HPUS.

INDICATIONS AND USAGE

Uses: Soothing homeopathic remedy for teething in babies and children.

WARNINGS

Warnings: If symptoms persist or worsen, consult a healthcare professional.

PREGNANCY OR BREAST FEEDING

If pregnant or breastfeeding, ask a health professional before use.

KEEP OUT OF REACH OF CHILDREN

Keep this and all medication out of reach of children.

OVERDOSAGE

In case of overdose, get medical help or contact a Poison Control Center right away.

DOSAGE AND ADMINISTRATION

Directions: Babies:Sprinkle 1 pinch on the tongue when needed. Repeat after 20 minutes for up to 10 doses if needed.

INACTIVE INGREDIENT

Inactive Ingredients: Citric acid, corn starch, potassium sorbate, sucrose.

PATIENT COUNSELING INFORMATION

The letters HPUS indicate that the components in this products are officially monographed in the Homeopathic Pharmacopoeia of the United States.

All Native Remedies health products are specially formulated by experts in the field of natural health and are manufactured according to the highest pharmaceutical standards for maximum safety and effectiveness. For more information, visit us at www.nativeremedies.com

Distributed by
Native Remedies, LLC
6531 Park of Commerce Blvd.
Suite 160
Boca Raton, Fl 33487
Phone: 1.877.289.1235
International:+1.561.999.8857

Contains no artificial flavors or artificial colors. No gluten added.